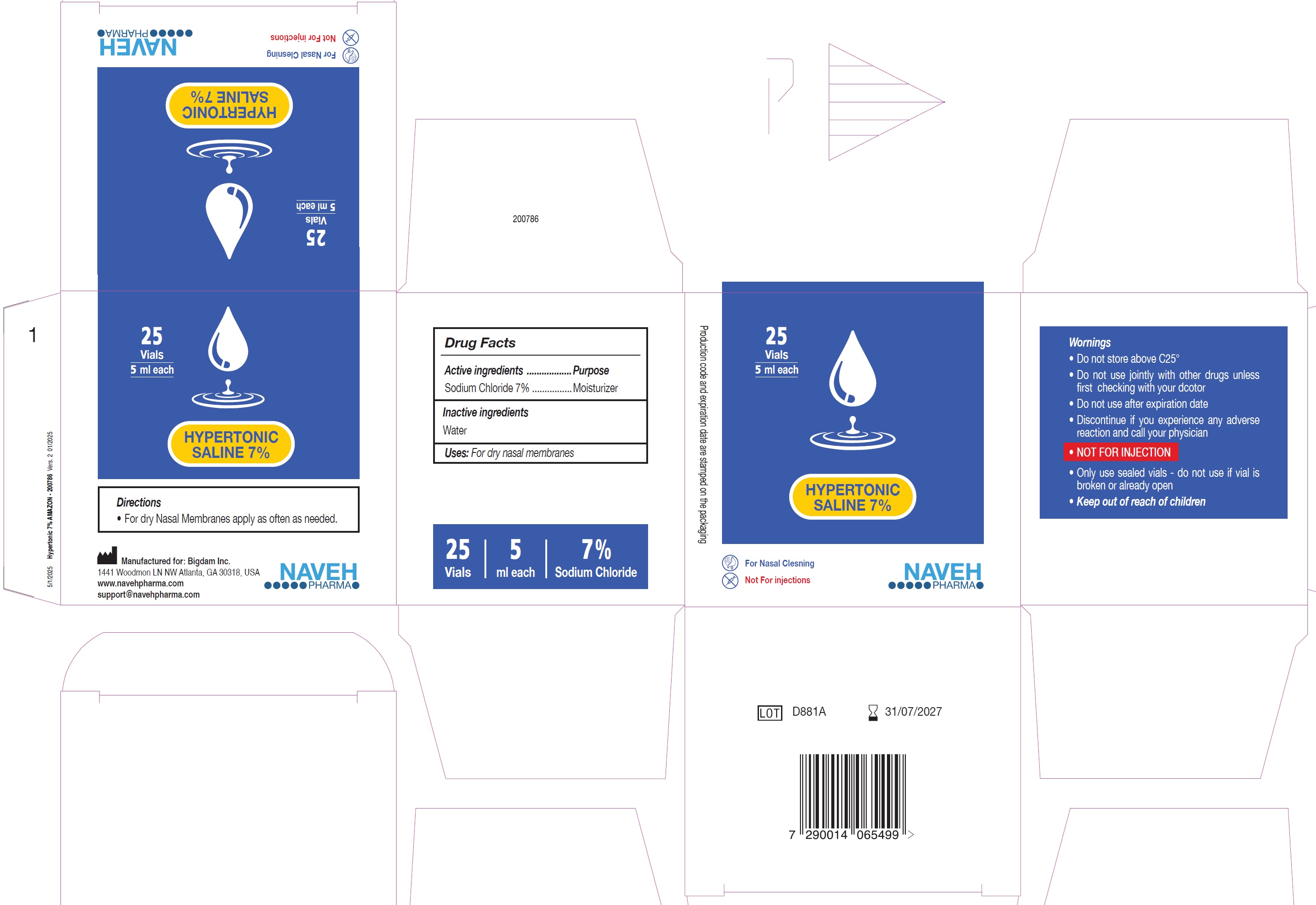 DRUG LABEL: Hypertonic Saline
NDC: 85202-000 | Form: LIQUID
Manufacturer: NAVEH PHARMA (1996) LTD
Category: otc | Type: HUMAN OTC DRUG LABEL
Date: 20250212

ACTIVE INGREDIENTS: SODIUM CHLORIDE 70 mg/1 mL
INACTIVE INGREDIENTS: WATER

Hypertonic Saline

Active ingredients

Sodium Chloride 7%

Purpose

Moisturizer

Inactive ingredients

Water

Uses:

For dry nasal membranes

Wornings

- Do not store above C25°

Do not use

- use jointly with other drugs unlessfirst checking with your dcotor
- Do not use after expiration date
- Discontinue if you experience any adverse reaction and call your physician
- NOT FOR INJECTION
- Only use sealed vials - do not use if vial is broken or already open

Directions

- For dry Nasal Membranes apply as often as needed.